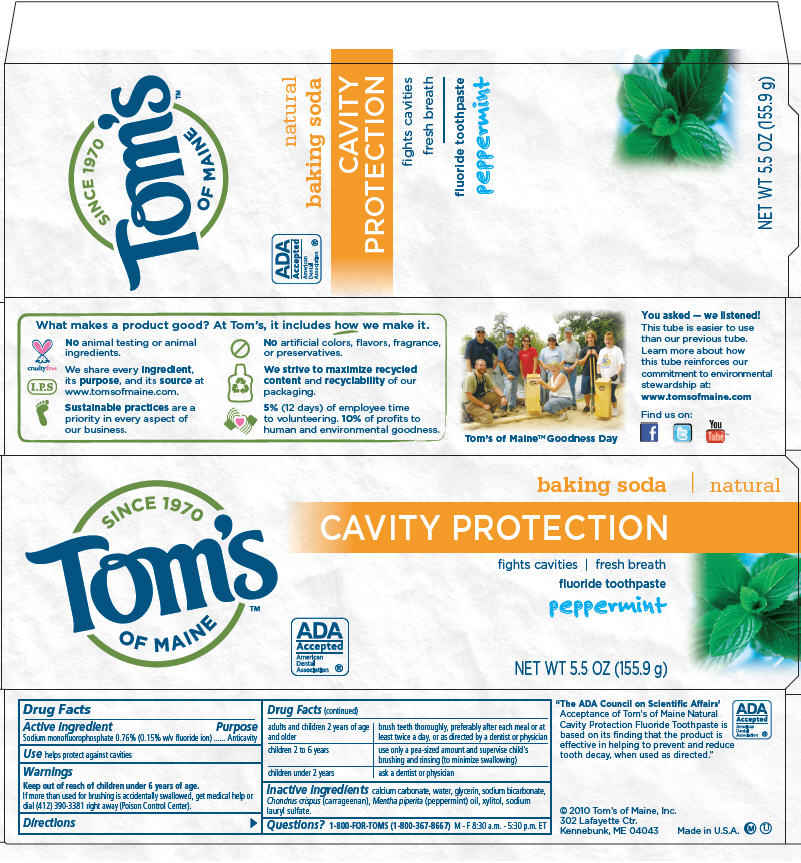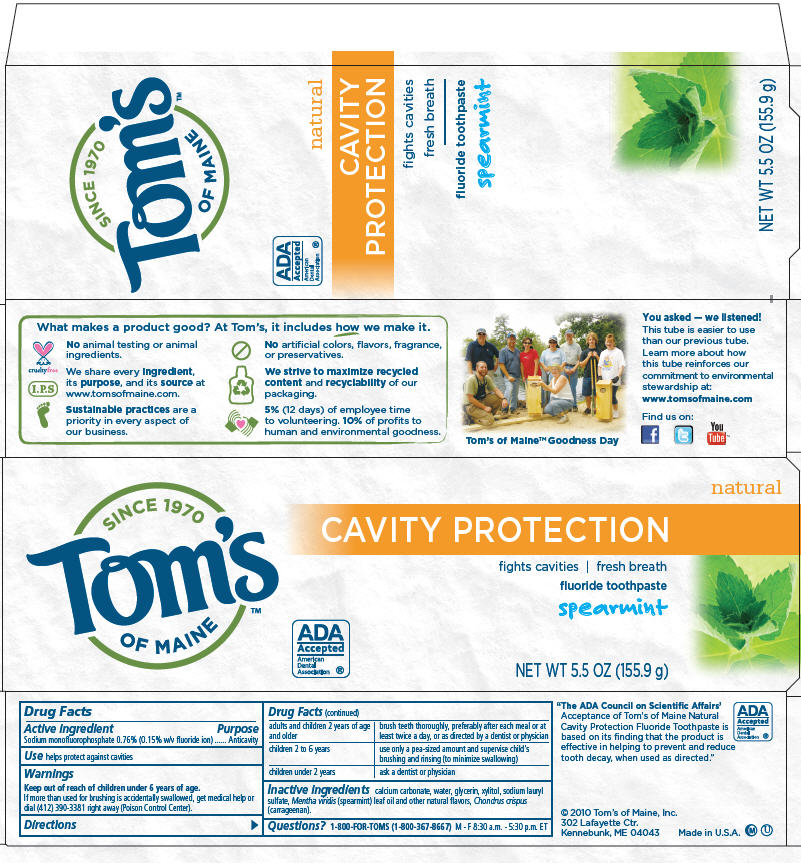 DRUG LABEL: Cavity Protection 
NDC: 51009-120 | Form: PASTE, DENTIFRICE
Manufacturer: Tom's of Maine, Inc.
Category: otc | Type: HUMAN OTC DRUG LABEL
Date: 20110510

ACTIVE INGREDIENTS: Sodium Monofluorophosphate 0.0076 g/1 g
INACTIVE INGREDIENTS: Calcium carbonate; Glycerin; Water; Sodium Bicarbonate; Carrageenan; Xylitol; Sodium Lauryl Sulfate; Peppermint oil

Tom's
OF MAINE
CAVITY PROTECTION
fluoride toothpaste

Drug Facts

Active ingredient

Sodium monofluorophosphate 0.76% (0.15% w/v fluoride ion)

Purpose

Anticavity

Use

helps protect against cavities

Warnings

Keep out of reach of children under 6 years of age.

If more than used for brushing is accidentally swallowed, get medical help or dial (412) 390-3381 right away (Poison Control Center).

Directions

adults and children 2 years of age and older | brush teeth thoroughly, preferably after each meal or at least twice a day, or as directed by a dentist or physician
children 2 to 6 years | use only a pea-sized amount and supervise child's brushing and rinsing (to minimize swallowing)
children under 2 years | ask a dentist or physician

Inactive ingredients

calcium carbonate, water, glycerin, sodium bicarbonate, Chondrus crispus (carrageenan), Mentha piperita (peppermint) oil, xylitol, sodium lauryl sulfate.

Questions?

1-800-FOR-TOMS (1-800-367-8667) M - F 8:30 a.m. - 5:30 p.m. ET

PRINCIPAL DISPLAY PANEL - 155.9 g Carton

SINCE 1970
Tom's
OF MAINE™

baking soda ∣ natural

CAVITY PROTECTION

fights cavities ∣ fresh breath

fluoride toothpaste

peppermint

ADA
Accepted
American
Dental
Association ®

NET WT 5.5 OZ (155.9 g)

PRINCIPAL DISPLAY PANEL - 155.9 g Carton

SINCE 1970
Tom's
OF MAINE™

natural

CAVITY PROTECTION

fights cavities ∣ fresh breath

fluoride toothpaste

spearmint

ADA
Accepted
American
Dental
Association ®

NET WT 5.5 OZ (155.9 g)